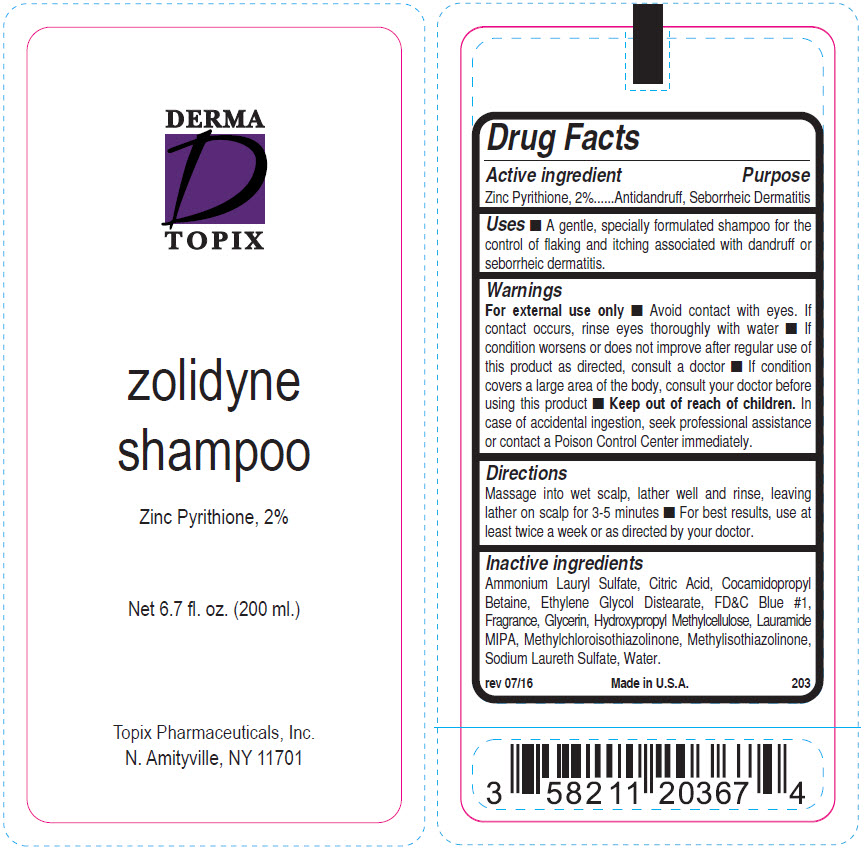 DRUG LABEL: Zolidyne
NDC: 51326-203 | Form: SHAMPOO
Manufacturer: Topiderm, Inc.
Category: otc | Type: HUMAN OTC DRUG LABEL
Date: 20191120

ACTIVE INGREDIENTS: PYRITHIONE ZINC 20 mg/1 mL
INACTIVE INGREDIENTS: AMMONIUM LAURYL SULFATE; CITRIC ACID MONOHYDRATE; COCAMIDOPROPYL BETAINE; GLYCOL DISTEARATE; FD&C BLUE NO. 1; GLYCERIN; HYPROMELLOSE, UNSPECIFIED; LAURIC ISOPROPANOLAMIDE; METHYLCHLOROISOTHIAZOLINONE; METHYLISOTHIAZOLINONE; SODIUM LAURETH-3 SULFATE; WATER

Zolidyne Shampoo

Drug Facts

Active ingredient

Zinc Pyrithione, 2%

Purpose

Antidandruff, Seborrheic Dermatitis

Uses

- A gentle, specially formulated shampoo for the control of flaking and itching associated with dandruff or seborrheic dermatitis.

Warnings

For external use only

- Avoid contact with eyes. If contact occurs, rinse eyes thoroughly with water
- If condition worsens or does not improve after regular use of this product as directed, consult a doctor
- If condition covers a large area of the body, consult your doctor before using this product

- Keep out of reach of children. In case of accidental ingestion, seek professional assistance or contact a Poison Control Center immediately.

Directions

Massage into wet scalp, lather well and rinse, leaving lather on scalp for 3-5 minutes

- For best results, use at least twice a week or as directed by your doctor.

Inactive ingredients

Ammonium Lauryl Sulfate, Citric Acid, Cocamidopropyl Betaine, Ethylene Glycol Distearate, FD&C Blue #1, Fragrance, Glycerin, Hydroxypropyl Methylcellulose, Lauramide MIPA, Methylchloroisothiazolinone, Methylisothiazolinone, Sodium Laureth Sulfate, Water.

PRINCIPAL DISPLAY PANEL - 200 ml Tube Label

DERMA
TOPIX

zolidyne
shampoo

Zinc Pyrithione, 2%

Net 6.7 fl. oz. (200 ml.)

Topix Pharmaceuticals, Inc.
N. Amityville, NY 11701